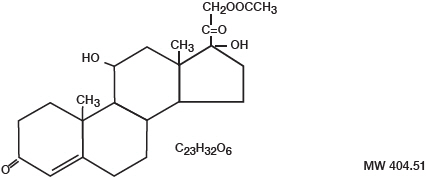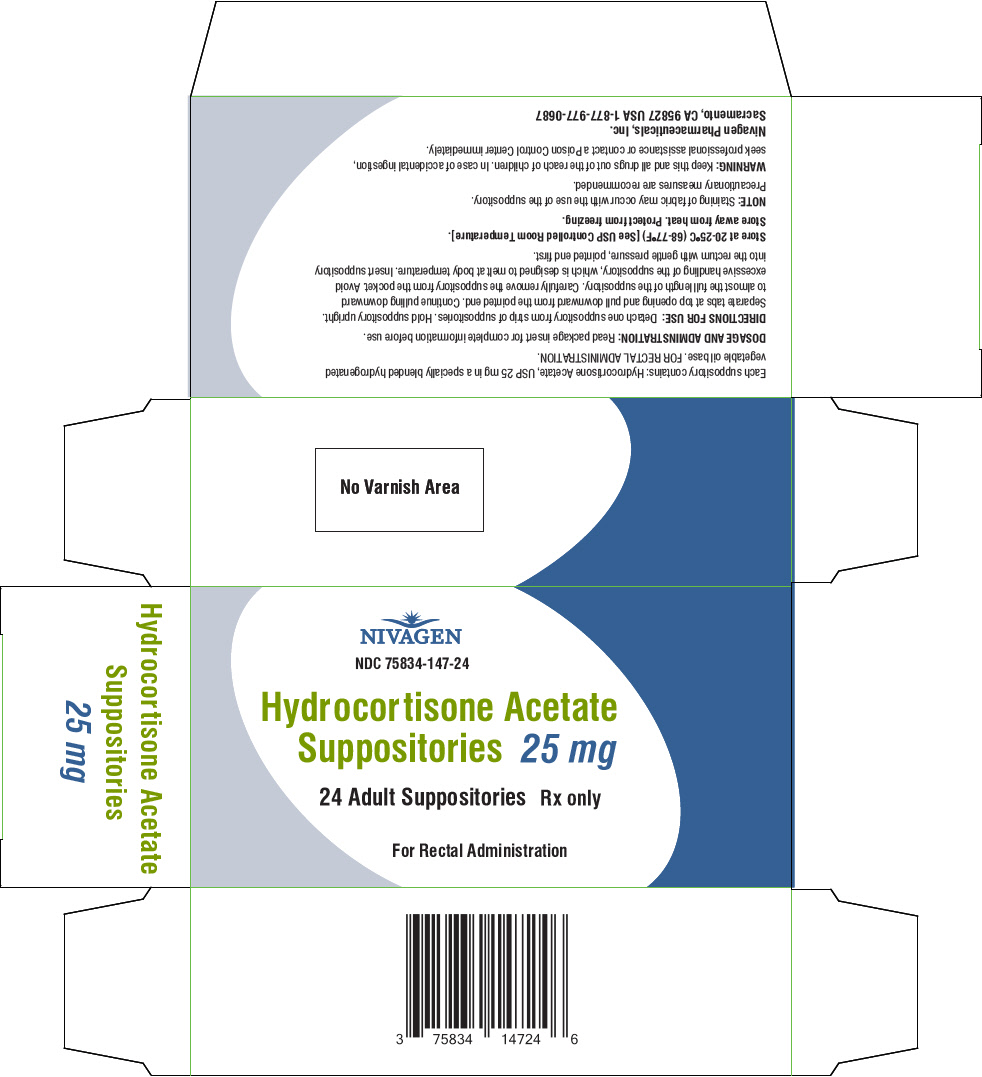 DRUG LABEL: HYDROCORTISONE ACETATE
NDC: 75834-147 | Form: SUPPOSITORY
Manufacturer: Nivagen Pharmaceuticals, Inc.
Category: prescription | Type: HUMAN PRESCRIPTION DRUG LABEL
Date: 20230828

ACTIVE INGREDIENTS: HYDROCORTISONE ACETATE 25 mg/1 1
INACTIVE INGREDIENTS: HYDROGENATED PALM KERNEL OIL

Hydrocortisone Acetate, 25 mg
Rectal Suppositories

DESCRIPTION

Hydrocortisone Acetate is a corticosteroid designated chemically as pregn-4-ene 3, 20-dione, 21-(acetyloxy)-11,17-dihydroxy-(11β) with the following structural formula:

Each rectal suppository contains hydrocortisone acetate, USP 25 mg in a specially blended hydrogenated vegetable oil base.

CLINICAL PHARMACOLOGY

In normal subjects, about 26% of hydrocortisone acetate is absorbed when the suppository is applied to the rectum. Absorption of hydrocortisone acetate may vary across abraded or inflamed surfaces. Topical steroids are primarily effective because of their anti-inflammatory, anti-pruritic and vasoconstrictive action.

INDICATIONS AND USAGE

Hydrocortisone acetate suppositories are indicated for use in inflamed hemorrhoids, post-irradiation (factitial) proctitis; as an adjunct in the treatment of chronic ulcerative colitis; cryptitis; and other inflammatory conditions of anorectum and pruritus ani.

CONTRAINDICATIONS

Hydrocortisone acetate suppositories are contraindicated in those patients having a history of hypersensitivity to hydrocortisone acetate or any of the components.

PRECAUTIONS

Do not use hydrocortisone acetate suppositories unless adequate proctologic examination is made.

If irritation develops, the product should be discontinued and appropriate therapy instituted.

In the presence of an infection, the use of an appropriate antifungal or antibacterial agent should be instituted. If a favorable response does not occur promptly, hydrocortisone acetate should be discontinued until the infection has been adequately controlled.

Carcinogenesis

No long term studies in animals have been performed to evaluate the carcinogenic potential of corticosteroid suppositories.

INFORMATION FOR PATIENTS

Staining of fabric may occur with use of the suppository. Precautionary measures are recommended.

PREGNANCY CATEGORY C

TERATOGENIC EFFECTS

In laboratory animals, topical steroids have been associated with an increase in the incidence of fetal abnormalities when gestating females have been exposed to rather low dosage levels. There are no adequate and well controlled studies in pregnant women.

Hydrocortisone acetate suppositories should only be used during pregnancy if the potential benefit justifies the risk to the fetus. Drugs of this class should not be used extensively on pregnant patients, in large amounts, or for prolonged periods of time.

It is not known whether this drug is excreted in human milk and because many drugs are excreted in human milk and because of the potential for serious adverse reactions in nursing infants from hydrocortisone acetate suppositories, a decision should be made whether to discontinue nursing or to discontinue the drug, taking into account the importance of the drug to the mother.

ADVERSE REACTIONS

The following local adverse reactions have been reported with hydrocortisone acetate suppositories: burning, itching, irritation, dryness, folliculitis, hypopigmentation, allergic contact dermatitis, secondary infection.

To report SUSPECTED ADVERSE REACTIONS, contact FDA at 1-800-FDA-1088 or www.fda.gov/medwatch.

Drug abuse and dependence have not been reported in patients treated with hydrocortisone acetate suppositories.

OVERDOSAGE

If signs and symptoms of systemic overdosage occur, discontinue use.

DOSAGE AND ADMINISTRATION

For rectal administration. Detach one suppository from strip of suppositories. Hold suppository upright. Separate tabs at top opening and pull downward from the pointed end. Continue pulling downward to almost the full length of the suppository. Carefully remove the suppository from the pocket. Avoid excessive handling of the suppository which is designed to melt at body temperature. Insert suppository into the rectum with gentle pressure, pointed end first. Insert one suppository in the rectum twice daily, morning and night for two weeks, in nonspecific proctitis. In more severe cases, one suppository three times a day or two suppositories twice daily. In factitial proctitis, the recommended duration of therapy is six to eight weeks or less, according to the response of the individual case.

HOW SUPPLIED

Boxes of 12 suppositories | NDC 75834-147-12
Boxes of 24 suppositories | NDC 75834-147-24

Rx only.

STORAGE AND HANDLING

Store at 20°-25°C (68°-77°F) [See USP Controlled Room Temperature]. Store away from heat. Protect From Freezing.

Manufactured for:
Nivagen Pharmaceuticals, Inc.
Sacramento, CA 95827 USA
Toll Free 1-877-977-0687

Rev. 04/20

PRINCIPAL DISPLAY PANEL - 25 mg Suppository Blister Pack Carton

NIVAGEN

NDC 75834-147-24

Hydrocortisone Acetate
Suppositories 25 mg

24 Adult Suppositories
Rx only

For Rectal Administration